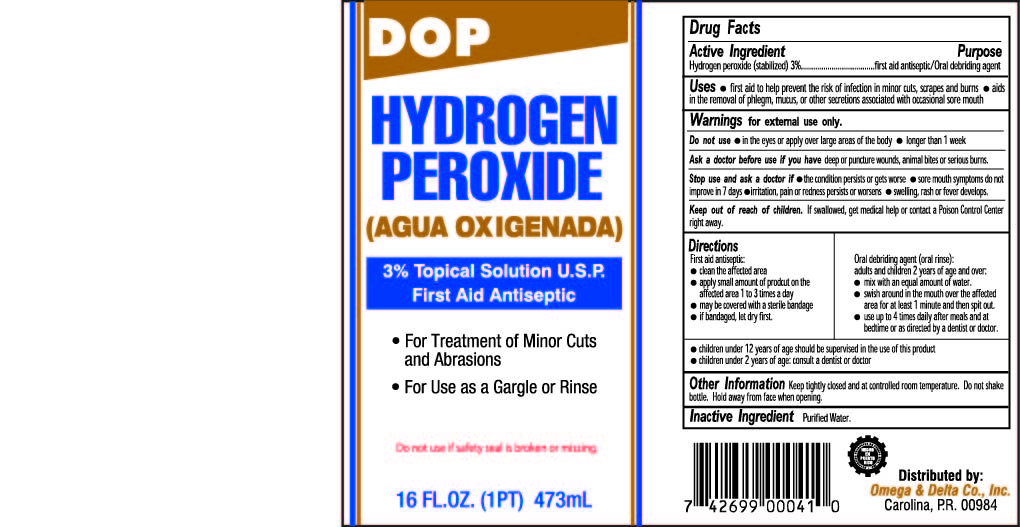 DRUG LABEL: DOP Hydrogen Peroxide 3%
NDC: 51048-040 | Form: LIQUID
Manufacturer: Omega & Delta Co. Inc.
Category: otc | Type: HUMAN OTC DRUG LABEL
Date: 20260121

ACTIVE INGREDIENTS: HYDROGEN PEROXIDE 3 g/100 mL
INACTIVE INGREDIENTS: WATER

DOP Hydrogen Peroxide 3% Topical Solution USP

Drug Facts

Active Ingredient

Hydrogen peroxide 3% (stabilized)

Purpose

first aid antiseptic / Oral debriding agent

Uses

- first aid to help prevent the risk of infection in minor cuts, scrapes and burns
- aids in the removal of phlegm, mucus, or other secretions associated with occasional sore mouth

Warnings

for external use only.

Do not use

- in the eyes or apply over large areas of the body
- longer than 1 week

Ask a doctor before use if you have

deep or puncture wounds, animal bites or serious burns.

Stop use and ask a doctor if

- the condition persists or gets worse
- sore mouth symptoms do not improve in 7 days
- irritation, pain or redness persists or worsens
- swelling, rash or fever develops

Keep out of reach of children

If swallowed, get medical help or contact a Poison Control Center right away

Directions

First aid antiseptic:

- clean the affected area
- apply small amount of product on the affected area 1 to 3 times a day
- may be covered with a sterile bandage
- if bandaged, let dry first

Oral debriding agent (oral rinse):

adults and children 2 years of age and over:

- mix with an equal amount of water
- swish around in the mouth over the affected area for at least 1 minute and then spit out
- use up to 4 times daily after meals and at bedtime or as directed by a dentist or doctor
- children under 12 years of age should be supervised in the use of this product
- children under 2 years of age: consult a dentist or a doctor

Other Information

Keep tightly closed and at a controlled room temperature. Do not shake bottle. Hold away from face when opening.

Inactive Ingredient

Purified Water

Distributed by:

Omega & Delta Co., Inc.

Carolina, P.R. 00984

Principal Display Panel

DOP

HYDROGEN

PEROXIDE

(AGUA OXIGENADA)

3% Topical Solution U.S.P.

First Aid Antiseptic

- For Treatment of Minor Cuts and Abrasions
- For Use as a Gargle or Rinse

Do not use if safety seal is broken or missing.

16 FL.OZ. (1PT) 473 mL